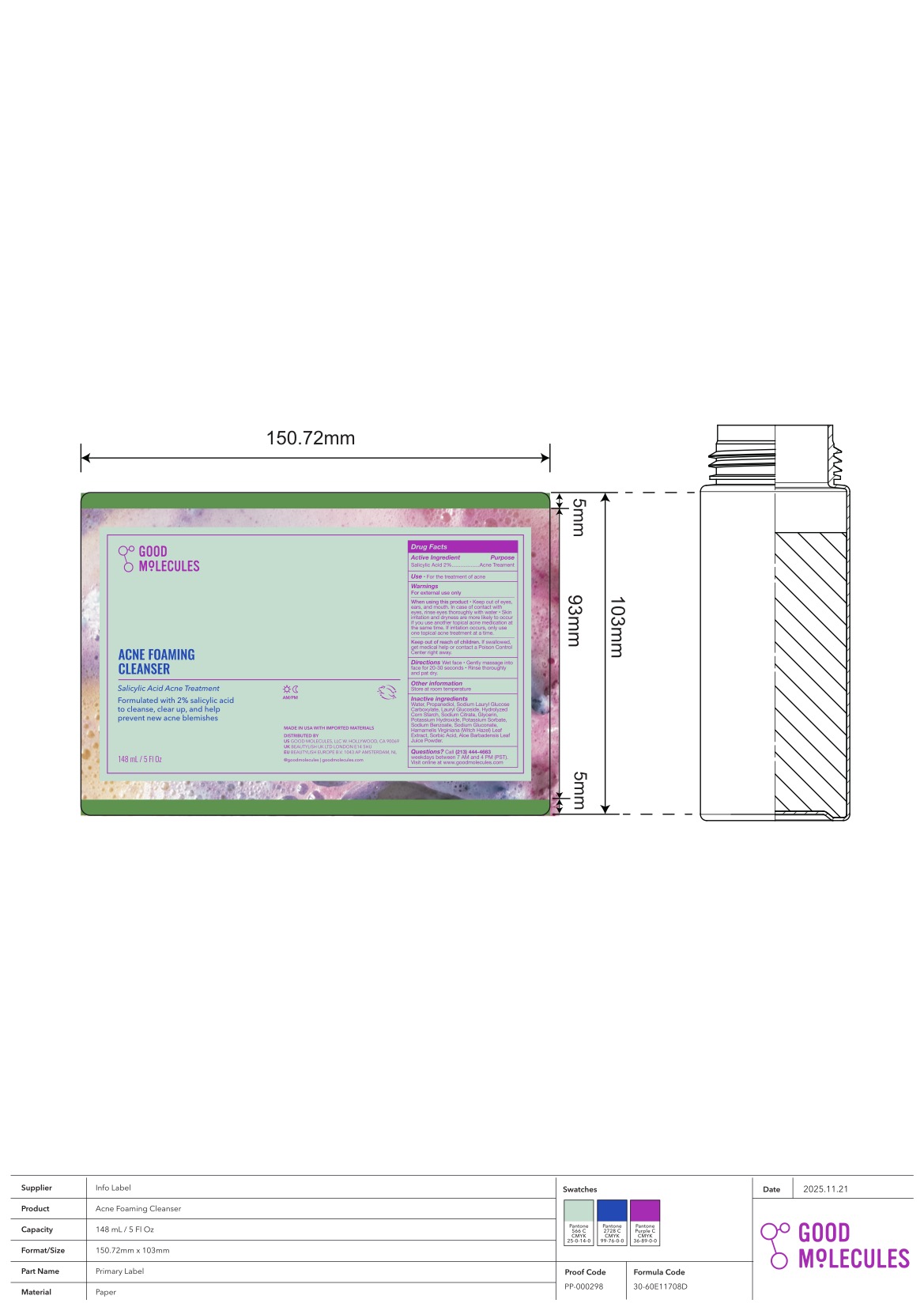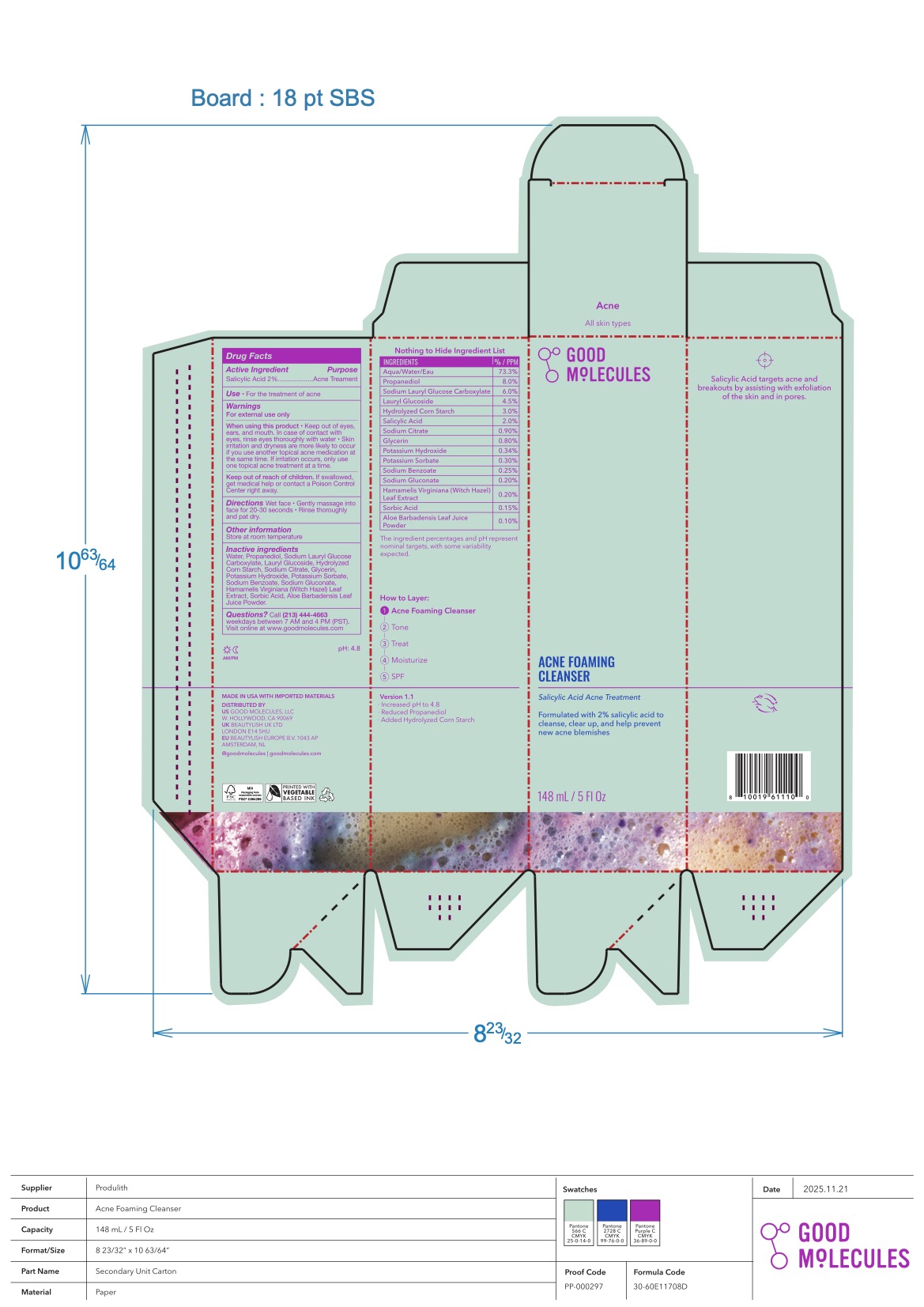 DRUG LABEL: Good Molecules Acne Foaming Cleanser
NDC: 64412-1005 | Form: GEL
Manufacturer: Twincraft Inc.
Category: otc | Type: HUMAN OTC DRUG LABEL
Date: 20260123

ACTIVE INGREDIENTS: SALICYLIC ACID 2 g/100 mL
INACTIVE INGREDIENTS: STARCH, CORN; SODIUM GLUCONATE; ALOE BARBADENSIS LEAF; WATER; LAURYL GLUCOSIDE; SODIUM LAURYL GLYCOL CARBOXYLATE; SODIUM CITRATE; POTASSIUM HYDROXIDE; SODIUM BENZOATE; SORBIC ACID; GLYCERIN; HAMAMELIS VIRGINIANA LEAF; POTASSIUM SORBATE; PROPANEDIOL

Purpose

Acne Treatment

Use

- For the treatment of acne

Active Ingredient

Salicylic Acid 2%

Warnings

For external use

When using this product

- Keep out of eyes, ears, and mouth. In case of contact with eyes, rinse eyes thoroughly with water.
- Skin irritation and dryness are more likely to occur if you use another topical acne medication at the same time. If irritation occurs, only use one topical acne treatment at a time.

Keep out of reach of children.

If swalloed, get medical help or contact a Poison Control Center right away.

Directions

- Wet face
- Gently massage into face for 20-30 seconds
- Rinse thoroughly and pat dry

Other information

Store at room temperature

Inactive ingredients

Water, Propanediol, Sodium Lauryl Glucose Carboxylate, Lauryl Glucoside, Hydrolyzed Corn Starch, Sodium Citrate, Glycerin, Potassium Hydroxide, Potassium Sorbate, Sodium Benzoate, Sodium Gluconate, Hamamelis Virginiana (Witch Hazel) Leaf Extract, Sorbic Acid, Aloe Barbadensis Leaf Juice Powder

Questions?

Call (213) 444 - 4663weekdays between 7 AM and 4 PM (PST). Visit online at www.goodmolecules.com